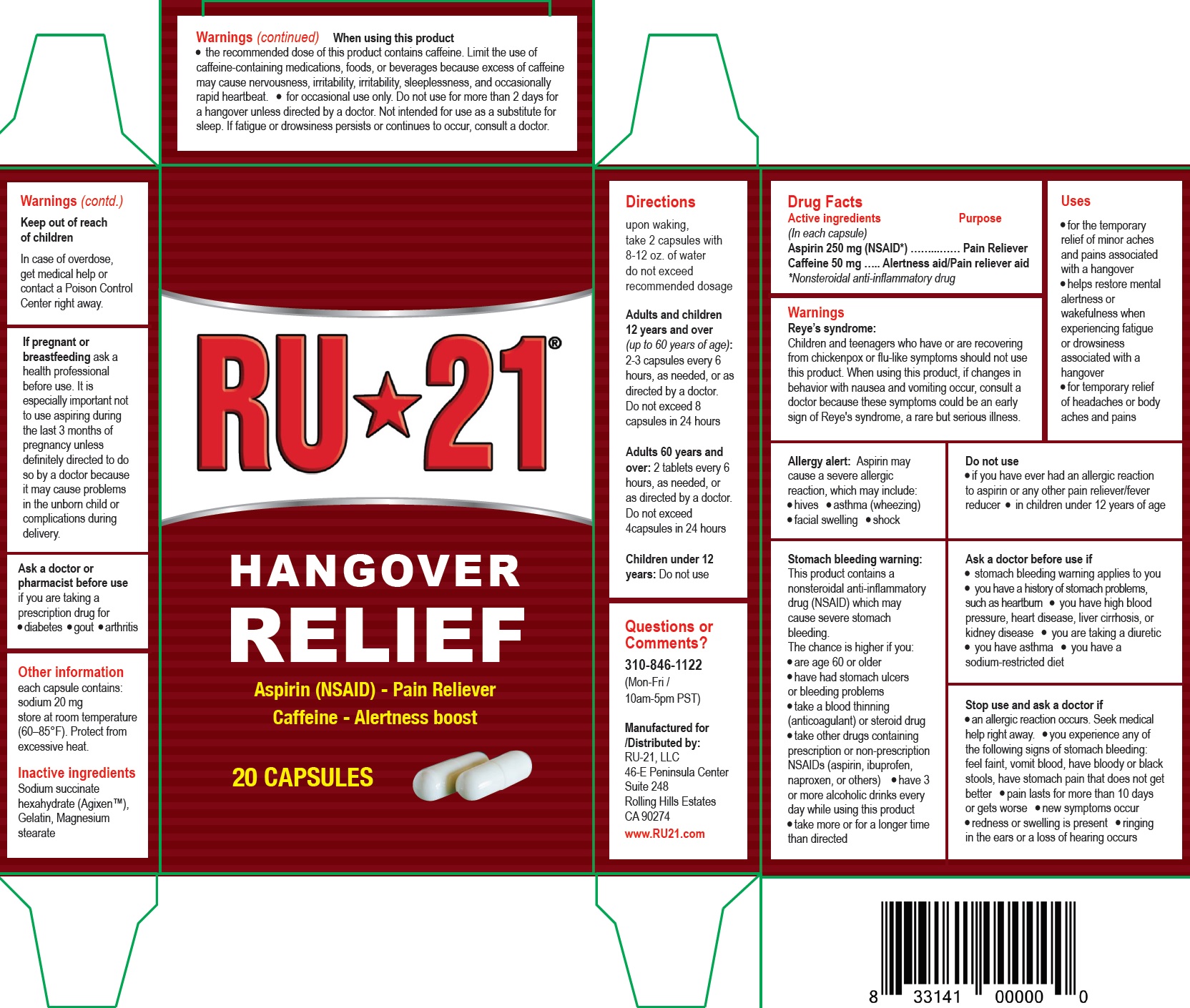 DRUG LABEL: RU-21 HANGOVER RELIEF
NDC: 73156-010 | Form: CAPSULE
Manufacturer: RU-21
Category: otc | Type: HUMAN OTC DRUG LABEL
Date: 20190621

ACTIVE INGREDIENTS: ASPIRIN 250 mg/1 1; CAFFEINE 50 mg/1 1
INACTIVE INGREDIENTS: SODIUM SUCCINATE HEXAHYDRATE; GELATIN; MAGNESIUM STEARATE

RU-21 HANGOVER RELIEF

Active ingredients (In each capsule)

Aspirin 250 mg (NSAID*)

Caffeine 50 mg

*Nonsteroidal anti-inflammatory drug

Purpose

Pain Reliever

Alertness aid/Pain reliever aid

Uses

• for the temporary relief of minor aches and pains associated with a hangover
• helps restore mental alertness or wakefulness when experiencing fatigue or drowsiness associated with a hangover
• for temporary relief of headaches or body aches and pains

Warnings

Reye’s syndrome: Children and teenagers who have or are recovering from chickenpox or flu-like symptoms should not use this product. When using this product, if changes in behavior with nausea and vomiting occur, consult a doctor because these symptoms could be an early sign of Reye's syndrome, a rare but serious illness.

Allergy alert: Aspirin may cause a severe allergic reaction, which may include: • hives • asthma (wheezing) • facial swelling • shock

Do not use

• if you have ever had an allergic reaction to aspirin or any other pain reliever/fever reducer

• in children under 12 years of age

Stomach bleeding warning:

This product contains a nonsteroidal anti-inflammatory drug (NSAID) which may cause severe stomach bleeding. The chance is higher if you:
• are age 60 or older
• have had stomach ulcers or bleeding problems
• take a blood thinning (anticoagulant) or steroid drug
• take other drugs containing prescription or non-prescription NSAIDs (aspirin, ibuprofen, naproxen, or others)

• have 3 or more alcoholic drinks every day while using this product
• take more or for a longer time than directed

Ask a doctor before use if

• stomach bleeding warning applies to you
• you have a history of stomach problems, such as heartburn • you have high blood pressure, heart disease, liver cirrhosis, or kidney disease

• you are taking a diuretic
• you have asthma • you have a sodium-restricted diet

Stop use and ask a doctor if

• an allergic reaction occurs. Seek medical help right away.

• you experience any of the following signs of stomach bleeding: feel faint, vomit blood, have bloody or black stools, have stomach pain that does not get better

• pain lasts for more than 10 days or gets worse

• new symptoms occur

• redness or swelling is present

• ringing in the ears or a loss of hearing occurs

When using this product

• the recommended dose of this product contains caffeine. Limit the use of caffeine-containing medications, foods, or beverages because excess of caffeine may cause nervousness, irritability, irritability, sleeplessness, and occasionally rapid heartbeat.

• for occasional use only. Do not use for more than 2 days for a hangover unless directed by a doctor. Not intended for use as a substitute for sleep. If fatigue or drowsiness persists or continues to occur, consult a doctor.

Keep out of reach of children

In case of overdose, get medical help or contact a Poison Control Center right away.

If pregnant or breastfeeding

ask a health professional before use. It is especially important not to use aspiring during the last 3 months of pregnancy unless definitely directed to do so by a doctor because it may cause problems in the unborn child or complications during delivery.

Ask a doctor or pharmacist before use

if you are taking a prescription drug for • diabetes • gout • arthritis

Directions

upon waking, take 2 capsules with 8-12 oz. of water do not exceed recommended dosage
Adults and children 12 years and over (up to 60 years of age): 2-3 capsules every 6 hours, as needed, or as directed by a doctor. Do not exceed 8 capsules in 24 hours
Adults 60 years and over: 2 tablets every 6 hours, as needed, or as directed by a doctor. Do not exceed 4capsules in 24 hours Children under 12 years: Do not use

Other information

each capsule contains: sodium 20 mg store at room temperature (60–85°F). Protect from excessive heat.

Inactive ingredients

Sodium succinate hexahydrate (Agixen™), Gelatin, Magnesium stearate

Questions or Comments?

310-846-1122 (Mon-Fri / 10am-5pm PST)

Manufactured for /Distributed by:
RU-21, LLC 46-E Peninsula Center Suite 248 Rolling Hills Estates CA 90274 www.RU21.com